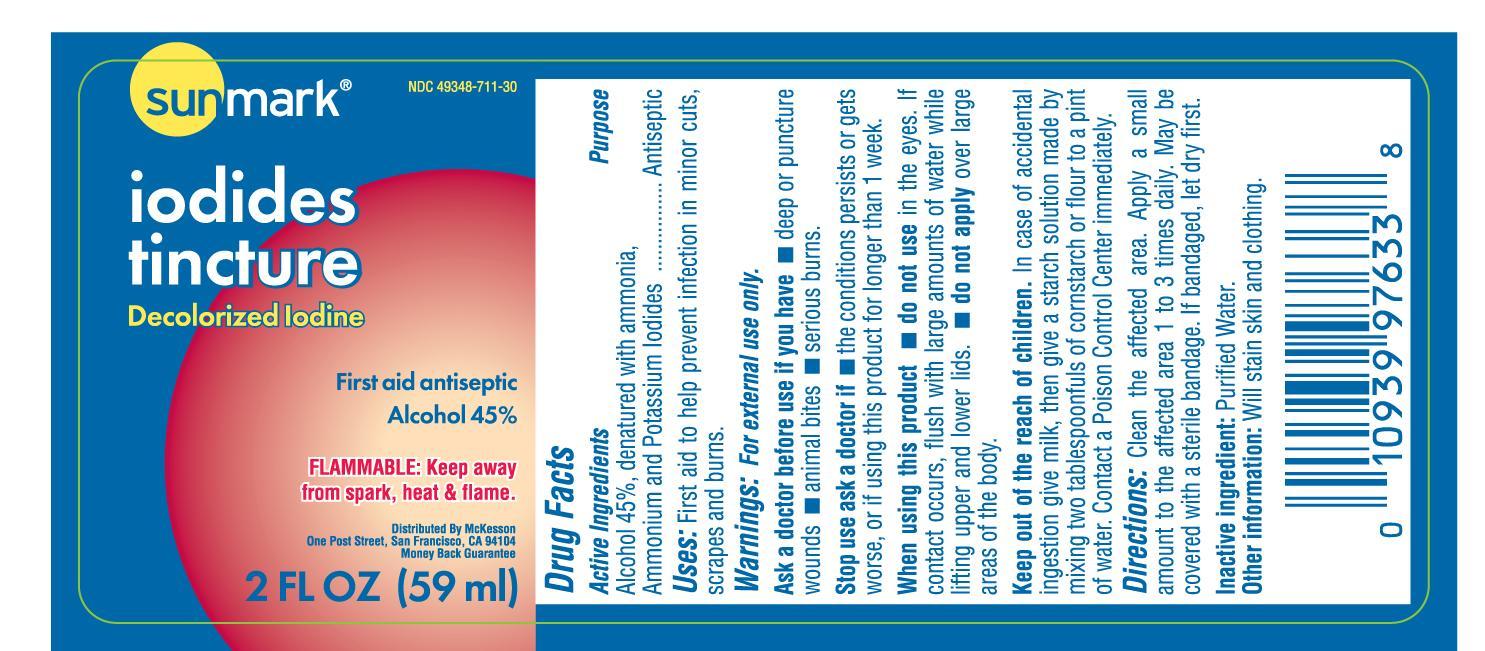 DRUG LABEL: Sunmark Iodides Tincture
NDC: 49348-711 | Form: LIQUID
Manufacturer: Strategic Sourcing Services LLC
Category: otc | Type: HUMAN OTC DRUG LABEL
Date: 20231219

ACTIVE INGREDIENTS: ALCOHOL 0.45 mL/1 mL
INACTIVE INGREDIENTS: WATER; AMMONIA; IODINE; POTASSIUM IODIDE

Sunmark Iodides Tincture

Drug Facts

Active ingredient

Ethyl Alcohol 48%

Purpose

First Aid Antiseptic

Use

first aid to help prevent infection in minor cuts, scrapes and burns.

Warnings

For external use only

When using this product

do not use in the eyes or apply over large areas of the body. In case of deep or puncture wounds, animal bites, or serious burns, consult a doctor.

Stop use and consult doctor if the

condition persists or gets worse. Do not use this product for longer than 1 week unless directed by a doctor.

Keep out of reach of children.

If swallowed, get medical help or contact a Poison Control Center right away.

Directions

- Clean the affected area.
- apply a small amount on the area 1 to 3 times daily.
- may be covered with sterile bandage.
- if bandaged, let dry first.

Other information

store at room temperature

Inactive ingredients

ammonium hydroxide, iodine, potassium iodide, and purified water

PRINCIPAL DISPLAY PANEL

Label